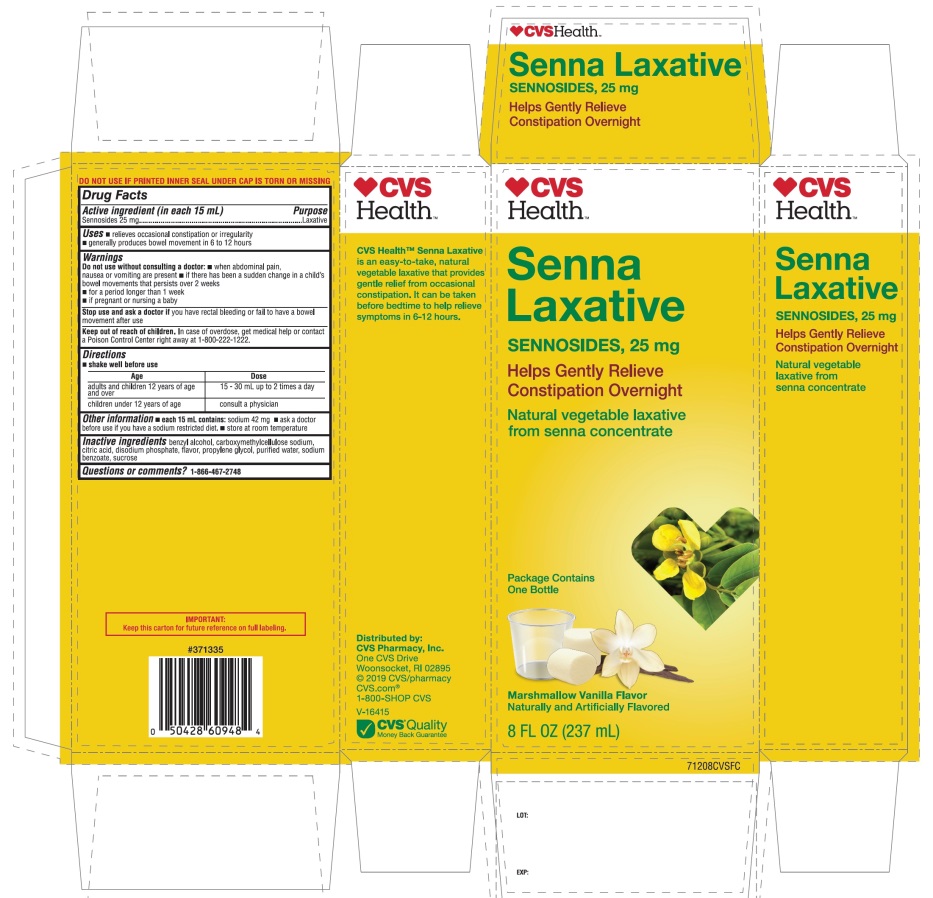 DRUG LABEL: CVS Senna Laxative
NDC: 69842-721 | Form: LIQUID
Manufacturer: CVS PHARMACY
Category: otc | Type: HUMAN OTC DRUG LABEL
Date: 20251209

ACTIVE INGREDIENTS: SENNOSIDES 25 mg/15 mL
INACTIVE INGREDIENTS: BENZYL ALCOHOL; CARBOXYMETHYLCELLULOSE SODIUM, UNSPECIFIED; ANHYDROUS CITRIC ACID; SODIUM PHOSPHATE, DIBASIC, ANHYDROUS; PROPYLENE GLYCOL; WATER; SODIUM BENZOATE; SUCROSE

CVS Senna Laxative Sennosides 25 mg

Drug Facts

Active Ingredient (in each 15 mL)

Sennosides 25 mg

Purpose

Laxative

Uses

- relieves occasional constipation (irregularity)
- generally produces bowel movement in 6-12 hours

Warnings

Do not use without consulting a doctor:

- when abdominal pain, nausea or vomiting are present
- If there has been a sudden change in child’s bowel movement that persists over 2 weeks
- For a period longer than 1 week
- If pregnant or nursing a baby

Stop use and ask a doctor if

you have rectal bleeding or fail to have a bowel movement after use.

Keep out of reach of children.In case of overdose, get medical help or contact a Poison Control Center right away at 1-800-222-1222.

Directions

- Shake well before use

Age | Dose
Adults and children 12 years of age and over | 15-30 mL up to 2 times a day
Children under 12 years of age | Consult a physician

Other information

- each 15 mL contains:sodium 42 mg
- ask a doctor before use if you have a sodium restricted diet.
- store at room temperature

SAFETY SEALED: DO NOT USE IF PRINTED INNER SEAL UNDER CAP IS TORN OR MISSING

Inactive ingredients

benzyl alcohol, carboxymethylcellulose sodium, citric acid, disodium phosphate, flavor, propylene glycol, purified water, sodium benzoate, sucrose.

Questions or comments?

1-866-467-2748

PRINCIPAL DISPLAY PANEL - CVS Senna Laxative

♥CVSHealth™

NDC 69842-721-08

SennaLaxative

SENNOSIDES, 25 mg

Helps Gently Relieves Constipation Overnight

Natural vegetable laxative from senna concentrate

Package Contains One Bottle

Marshmallow Vanilla Flavor

Naturally and Artificially Flavor

8 FL OZ (237 mL)

CVS Health™ Senna Laxative is an easy-to-take, natural vegetable laxative that provides gentle relief from occasional constipation. It can be taken before bedtime to help relieve symptoms in 6-12 hours.

Distributed by:

CVS Pharmacy, Inc.

One CVS Drive

Woonsocket, RI 02895

© 2019 CVS/pharmacy

CVS.com®

1-800-SHOP CVS

V-16415

CVS®Quality

Money Back Guarantee

IMPORTANT: Keep the carton for future reference on full labeling.